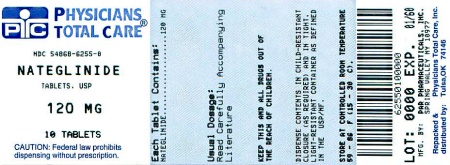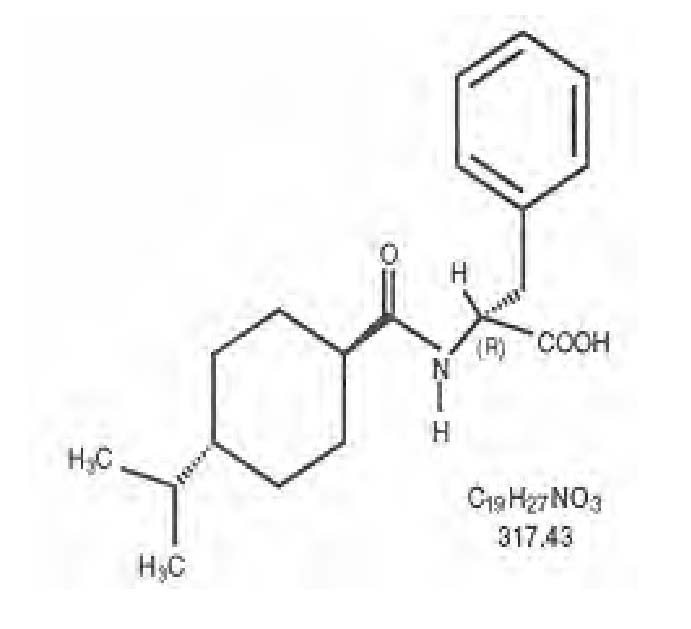 DRUG LABEL: Nateglinide 
NDC: 54868-6255 | Form: TABLET, COATED
Manufacturer: Physicians Total Care, Inc.
Category: prescription | Type: HUMAN PRESCRIPTION DRUG LABEL
Date: 20111212

ACTIVE INGREDIENTS: NATEGLINIDE 120 mg/1 1
INACTIVE INGREDIENTS: COLLOIDAL SILICON DIOXIDE; CROSCARMELLOSE SODIUM; LACTOSE MONOHYDRATE; MAGNESIUM STEARATE; CELLULOSE, MICROCRYSTALLINE; POVIDONE; FD&C YELLOW NO. 6

DESCRIPTION

Nateglinide Tablets, USP are an oral antidiabetic agent used in the management of Type 2 diabetes mellitus [also known as non-insulin dependent diabetes mellitus (NIDDM) or adult-onset diabetes]. Nateglinide,(-)-N-[(trans-4-isopropylcyclohexane)carbonyl]-D-phenylalanine, is structurally unrelated to the oral sulfonylurea insulin secretagogues.

The structural formula is as shown

Nateglinide is a white powder with a molecular weight of 317.43. It is freely soluble in methanol, ethanol, and chloroform, soluble in ether, sparingly soluble in acetonitrile and octanol, and practically insoluble in water. Nateglinide biconvex tablets contain 60 mg, or 120 mg, of nateglinide for oral administration.

Inactive Ingredients: colloidal silicon dioxide, croscarmellose sodium, lactose monohydrate, magnesium stearate, microcrystalline cellulose, povidone, pregelatinized starch. The 60 mg also contains iron oxide red, polyethylene glycol, polyvinyl alcohol, talc, and titanium dioxide. In addition, the 120 mg contains FD&C Yellow #6/Sunset Yellow Aluminum Lake, iron oxide yellow.

CLINICAL PHARMACOLOGY

Mechanism of Action

Nateglinide is an amino-acid derivative that lowers blood glucose levels by stimulating insulin secretion from the pancreas. This action is dependent upon functioning beta-cells in the pancreatic islets. Nateglinide interacts with the ATP-sensitive potassium (K+ ATP) channel on pancreatic beta-cells. The subsequent depolarization of the beta cell opens the calcium channel, producing calcium influx and insulin secretion. The extent of insulin release is glucose dependent and diminishes at low glucose levels. Nateglinide is highly tissue selective with low affinity for heart and skeletal muscle.

Pharmacokinetics

Absorption

Following oral administration immediately prior to a meal, nateglinide is rapidly absorbed with mean peak plasma drug concentrations (Cmax) generally occurring within 1 hour (Tmax) after dosing. When administered to patients with Type 2 diabetes over the dosage range 60 mg to 240 mg three times a day for one week, nateglinide demonstrated linear pharmacokinetics for both AUC (area under the time/plasma concentration curve) and Cmax. Tmax was also found to be independent of dose in this patient population. Absolute bioavailability is estimated to be approximately 73%. When given with or after meals, the extent of nateglinide absorption (AUC) remains unaffected. However, there is a delay in the rate of absorption characterized by a decrease in Cmax and a delay in time to peak plasma concentration (Tmax). Plasma profiles are characterized by multiple plasma concentration peaks when nateglinide is administered under fasting conditions. This effect is diminished when nateglinide is taken prior to a meal.

Distribution

Based on data following intravenous (IV) administration of nateglinide, the steady-state volume of distribution of nateglinide is estimated to be approximately 10 liters in healthy subjects. Nateglinide is extensively bound (98%) to serum proteins, primarily serum albumin, and to a lesser extent α1 acid glycoprotein. The extent of serum protein binding is independent of drug concentration over the test range of 0.1 to 10 mcg/mL.

Metabolism

Nateglinide is metabolized by the mixed-function oxidase system prior to elimination. The major routes of metabolism are hydroxylation followed by glucuronide conjugation. The major metabolites are less potent antidiabetic agents than nateglinide. The isoprene minor metabolite possesses potency similar to that of the parent compound nateglinide.

In vitro data demonstrate that nateglinide is predominantly metabolized by cytochrome P450 isoenzymes CYP2C9 (70%) and CYP3A4 (30%).

Excretion

Nateglinide and its metabolites are rapidly and completely eliminated following oral administration. Within 6 hours after dosing, approximately 75% of the administered ^14C-nateglinide was recovered in the urine. Eighty-three percent of the ^14C-nateglinide was excreted in the urine with an additional 10% eliminated in the feces. Approximately 16% of the ^14C-nateglinide was excreted in the urine as parent compound. In all studies of healthy volunteers and patients with Type 2 diabetes, nateglinide plasma concentrations declined rapidly with an average elimination half-life of approximately 1.5 hours. Consistent with this short elimination half-life, there was no apparent accumulation of nateglinide upon multiple dosing of up to 240 mg three times daily for 7 days.

Drug Interactions

In vitro drug metabolism studies indicate that nateglinide is predominantly metabolized by the cytochrome P450 isozyme CYP2C9 (70%) and to a lesser extent CYP3A4 (30%). Nateglinide is a potential inhibitor of the CYP2C9 isoenzyme in vivo as indicated by its ability to inhibit the in vitro metabolism of tolbutamide. Inhibition of CYP3A4 metabolic reactions was not detected in in vitro experiments.

Glyburide: In a randomized, multiple-dose crossover study, patients with Type 2 diabetes were administered 120 mg nateglinide three times a day before meals for 1 day in combination with glyburide 10 mg daily. There were no clinically relevant alterations in the pharmacokinetics of either agent.

Metformin: When nateglinide 120 mg three times daily before meals was administered in combination with metformin 500 mg three times daily to patients with Type 2 diabetes, there were no clinically relevant changes in the pharmacokinetics of either agent.

Digoxin: When nateglinide 120 mg before meals was administered in combination with a single 1 mg dose of digoxin to healthy volunteers, there were no clinically relevant changes in the pharmacokinetics of either agent.

Warfarin: When healthy subjects were administered nateglinide 120 mg three times daily before meals for four days in combination with a single dose of warfarin 30 mg on day 2, there were no alterations in the pharmacokinetics of either agent. Prothrombin time was not affected.

Diclofenac: Administration of morning and lunch doses of nateglinide 120 mg in combination with a single 75 mg dose of diclofenac in healthy volunteers resulted in no significant changes to the pharmacokinetics of either agent.

Special Populations

Geriatric: Age did not influence the pharmacokinetic properties of nateglinide. Therefore, no dose adjustments are necessary for elderly patients.

Gender: No clinically significant differences in nateglinide pharmacokinetics were observed between men and women. Therefore, no dose adjustment based on gender is necessary.

Race: Results of a population pharmacokinetic analysis including subjects of Caucasian, Black, and other ethnic origins suggest that race has little influence on the pharmacokinetics of nateglinide.

Renal Impairment: Compared to healthy matched subjects, patients with Type 2 diabetes and moderate-to-severe renal insufficiency (CrCl 15 to 50 mL/min) not on dialysis displayed similar apparent clearance, AUC and Cmax. Patients with Type 2 diabetes and renal failure on dialysis exhibited reduced overall drug exposure. However, hemodialysis patients also experienced reductions in plasma protein binding compared to the matched healthy volunteers.

Hepatic Impairment: The peak and total exposure of nateglinide in non-diabetic subjects with mild hepatic insufficiency were increased by 30% compared to matched healthy subjects. Nateglinide should be used with caution in patients with chronic liver disease. (See PRECAUTIONS, Hepatic Impairment.)

Pharmacodynamics

Nateglinide is rapidly absorbed and stimulates pancreatic insulin secretion within 20 minutes of oral administration. When nateglinide is dosed three times daily before meals there is a rapid rise in plasma insulin, with peak levels approximately 1 hour after dosing and a fall to baseline by 4 hours after dosing.

In a double-blind, controlled clinical trial in which nateglinide was administered before each of three meals, plasma glucose levels were determined over a 12-hour, daytime period after 7 weeks of treatment. Nateglinide was administered 10 minutes before meals. The meals were based on standard diabetic weight maintenance menus with the total caloric content based on each subject’s height. Nateglinide produced statistically significant decreases in fasting and postprandial glycemia compared to placebo.

CLINICAL STUDIES

A total of 3,566 patients were randomized in nine double-blind, placebo-or active-controlled studies 8 to 24 weeks in duration to evaluate the safety and efficacy of nateglinide. 3,513 patients had efficacy values beyond baseline. In these studies nateglinide was administered up to 30 minutes before each of three main meals daily.

Nateglinide Monotherapy Compared to Placebo

In a randomized, double-blind, placebo-controlled, 24-week study, patients with Type 2 diabetes with HbA1c ≥6.8% on diet alone were randomized to receive either nateglinide (60 mg or 120 mg three times daily before meals) or placebo. Baseline HbA1c ranged from 7.9% to 8.1% and 77.8% of patients were previously untreated with oral antidiabetic therapy. Patients previously treated with antidiabetic medications were required to discontinue that medication for at least 2 months before randomization. The addition of nateglinide before meals resulted in statistically significant reductions in mean HbA1c and mean fasting plasma glucose (FPG) compared to placebo (see Table 1). The reductions in HbA1c and FPG were similar for patients naïve to, and those previously exposed to, antidiabetic medications.

In this study, one episode of severe hypoglycemia (plasma glucose <36 mg/dL) was reported in a patient treated with nateglinide 120 mg three times daily before meals. No patients experienced hypoglycemia that required third party assistance. Patients treated with nateglinide had statistically significant mean increases in weight compared to placebo (see Table 1).

In another randomized, double-blind, 24-week, active-and placebo-controlled study, patients with Type 2 diabetes were randomized to receive nateglinide (120 mg three times daily before meals), metformin 500 mg (three times daily), a combination of nateglinide 120 mg (three times daily before meals) and metformin 500 mg (three times daily), or placebo. Baseline HbA1c ranged from 8.3% to 8.4%. Fifty-seven percent of patients were previously untreated with oral antidiabetic therapy. Nateglinide monotherapy resulted in significant reductions in mean HbA1c and mean FPG compared to placebo that were similar to the results of the study reported above (see Table 2).

Table 1: Endpoint results for a 24-week, fixed dose study of Nateglinide monotherapy
HbA1c (%) | Placebo N=168 | Nateglinide 60 mg three times daily before meals N=167 | Nateglinide 120 mg three times daily before meals N=168
Baseline (mean) Change from baseline (mean) Difference from placebo (mean | 8.0 +0.2 | 7.9 -0.3 -0.5a | 8.1 -0.5 -0.7a
FPG (mg/dL) | N=172 | N=171 | N=169
Baseline (mean) Change from baseline (mean) Difference from placebo (mean) | 167.9 +9.1 | 161.0 +0.4 -8.7a | 166.5 -4.5 -13.6a
Weight (kg) | N=170 | N=169 | N=166
Baseline (mean) Change from baseline (mean) Difference from placebo (mean) | 85.8 -0.7 | 83.7 +0.3 +1.0a | 86.3 +0.9 +1.6a
a p-value ≤0.004

Nateglinide Monotherapy Compared to Other Oral Antidiabetic Agents

Glyburide

In a 24-week, double-blind, active-controlled trial, patients with Type 2 diabetes who had been on a sulfonylurea for ≥ 3 months and who had a baseline HbA1c ≥6.5% were randomized to receive nateglinide (60 mg or 120 mg three times daily before meals) or glyburide 10 mg once daily. Patients randomized to nateglinide had significant increases in mean HbA1c and mean FPG at endpoint compared to patients randomized to glyburide.

Metformin

In another randomized, double-blind, 24-week, active- and placebo-controlled study, patients with Type 2 diabetes were randomized to receive nateglinide (120 mg three times daily before meals), metformin 500 mg (three times daily), a combination of nateglinide 120 mg (three times daily before meals) and metformin 500 mg (three times daily), or placebo. Baseline HbA1c ranged from 8.3% to 8.4%. Fifty-seven percent of patients were previously untreated with oral antidiabetic therapy. Patients previously treated with antidiabetic medications were required to discontinue medication for at least 2 months before randomization. The reductions in mean HbA1c and mean FPG at endpoint with metformin monotherapy were significantly greater than the reductions in these variables with nateglinide monotherapy (see Table 2). Relative to placebo, nateglinide monotherapy was associated with significant increases in mean weight whereas metformin monotherapy was associated with significant decreases in mean weight. Among the subset of patients naïve to antidiabetic therapy, the reductions in mean HbA1c and mean FPG for nateglinide monotherapy were similar to those for metformin monotherapy (see Table 2). Among the subset of patients previously treated with other antidiabetic agents, primarily glyburide, HbA1c in the nateglinide monotherapy group increased slightly from baseline, whereas HbA1c was reduced in the metformin monotherapy group (see Table 2).

Nateglinide Combination Therapy

Metformin

In the active and placebo-controlled study of metformin and nateglinide described above, the combination of nateglinide and metformin resulted in statistically significantly greater reductions in HbA1c and FPG compared to either nateglinide or metformin monotherapy (see Table 2). Nateglinide, alone or in combination with metformin, significantly reduced the prandial glucose elevation form pre-meal to 2-hours post-meal compared to placebo and metformin alone.

In this study, one episode of severe hypoglycemia (plasma glucose ≤36 mg/dL) was reported in a patient receiving the combination of nateglinide and metformin and four episodes of severe hypoglycemia were reported in a single patient in the metformin treatment arm. No patient experienced an episode of hypoglycemia that required third party assistance. Compared to placebo, nateglinide monotherapy was associated with a statistically significant increase in weight, while no significant change in weight was observed with combined nateglinide and metformin therapy (see Table 2).

In another 24-week, double-blind, placebo-controlled trial, patients with Type 2 diabetes with HbA1c ≥6.8% after treatment with metformin (≥1500 mg daily for ≥1 month) were first entered into a four-week run-in period of metformin monotherapy (2000 mg daily) and then randomized to receive nateglinide (60 mg or 120 mg three times daily before meals) or placebo in addition to metformin. Combination therapy with nateglinide and metformin was associated with statistically significantly greater reductions in HbA1c compared to metformin monotherapy (-0.4% and -0.6% for nateglinide 60 mg and nateglinide 120 mg plus metformin, respectively).

Table 2: Endpoint results for a 24-week study of Nateglinide monotherapy and combination with metformin
HbA1c (%) All | Placebo N=160 | Nateglinide 120 mg three times daily before meals N=171 | Metformin 500 mg three times daily N=172 | Nateglinide 120 mg before meals plus Metformin* N=162
Baseline (mean) Change from baseline (mean) Difference from placebo Naïve | 8.3 +0.4 N=98 | 8.3 -0.4bc -0.8a N=99 | 8.4 -0.8c -1.2a N=98 | .4 -1.5 -1.9a N=81
Baseline (mean) Change from baseline (mean) Difference from placebo Non-Naïve | 8.2 +0.3 N=62 | 8.1 -0.7c -1.0a N=72 | 8.3 -0.8c -1.1a N=74 | 8.2 -1.6 -1.9a N=81
Baseline (mean) Change from baseline (mean) Difference from placebo FPG (mg/dL) All | 8.3 +0.6 N=166 | 8.5 +0.004bc -0.6a N=173 | 8.7 -0.8c -1.4a N=174 | 8.7 -1.4 -2.0a N=167
Baseline (mean) Change from baseline (mean) Difference from placebo Weight (kg) All | 194.0 +8.0 N=160 | 196.5 -13.1bc -21.1a N=169 | 196.0 -30.0c -38.0a N=169 | 197.7 -44.9 -52.9a N=160
Baseline (mean) Change from baseline (mean) Difference from placebo | 85.0 -0.4 | 85.0 +0.9 bc +1.3 a | 86.0 -0.1 +0.3 | 87.4 +0.2 +0.6
a p-value ≤0.05 vs. placebob
p-value ≤0.03 vs. metformin
c p-value ≤0.05 vs. combination
* Metformin was administered three times daily

Rosiglitazone

A 24-week, double blind multicenter, placebo-controlled trial was performed in patients with Type 2 diabetes not adequately controlled after a therapeutic response to rosiglitazone monotherapy 8 mg daily. The addition of nateglinide (120 mg three times per day with meals) was associated with statistically significantly greater reductions in HbA1c compared to rosiglitazone monotherapy. The difference was -0.77% at 24 weeks. The mean change in weight from baseline was about +3 kg for patients treated with nateglinide plus rosiglitazone vs about +1 kg for patients treated with placebo plus rosiglitazone.

Glyburide

In a 12-week study of patients with Type 2 diabetes inadequately controlled on glyburide 10 mg once daily, the addition of nateglinide (60 mg or 120 mg three times daily before meals) did not produce any additional benefit.

INDICATIONS AND USAGE

Nateglinide Tablets are indicated as an adjunct to diet and exercise to improve glycemic control in adults with Type 2 diabetes mellitus.

CONTRAINDICATIONS

Nateglinide Tablets are contraindicated in patients with:

1. Known hypersensitivity to the drug or its inactive ingredients.
2. Type 1 diabetes.
3. Diabetic ketoacidosis. This condition should be treated with insulin.

PRECAUTIONS

Macrovascular Outcomes: There have been no clinical studies establishing conclusive evidence of macrovascular risk reduction with nateglinide or any other antidiabetic drug.

Hypoglycemia: All oral blood glucose lowering drugs that are absorbed systemically are capable of producing hypoglycemia. The frequency of hypoglycemia is related to the severity of the diabetes, the level of glycemic control, and other patient characteristics. Geriatric patients, malnourished patients, and those with adrenal or pituitary insufficiency or severe renal impairment are more susceptible to the glucose lowering effect of these treatments. The risk of hypoglycemia may be increased by strenuous physical exercise, ingestion of alcohol, insufficient caloric intake on an acute or chronic basis, or combinations with other oral antidiabetic agents. Hypoglycemia may be difficult to recognize in patients with autonomic neuropathy and/or those who use beta-blockers. Nateglinide should be administered prior to meals to reduce the risk of hypoglycemia. Patients who skip meals should also skip their scheduled dose of nateglinide to reduce the risk of hypoglycemia.

Hepatic Impairment: Nateglinide should be used with caution in patients with moderate-to-severe liver disease because such patients have not been studied.

Loss of Glycemic Control

Transient loss of glycemic control may occur with fever, infection, trauma, or surgery. Insulin therapy may be needed instead of nateglinide therapy at such times. Secondary failure, or reduced effectiveness of nateglinide over a period of time, may occur.

Information for Patients

Patients should be informed of the potential risks and benefits of nateglinide and of alternative modes of therapy. The risks and management of hypoglycemia should be explained. Patients should be instructed to take nateglinide 1 to 30 minutes before ingesting a meal, but to skip their scheduled dose if they skip the meal so that the risk of hypoglycemia will be reduced. Drug interactions should be discussed with patients. Patients should be informed of potential drug-drug interactions with nateglinide.

Laboratory Tests

Response to therapies should be periodically assessed with glucose values and HbA1c levels.

Drug Interactions

Nateglinide is highly bound to plasma proteins (98%), mainly albumin. In vitro displacement studies with highly protein-bound drugs such as furosemide, propranolol, captopril, nicardipine, pravastatin, glyburide, warfarin, phenytoin, acetylsalicylic acid, tolbutamide, and metformin showed no influence on the extent of nateglinide protein binding. Similarly, nateglinide had no influence on the serum protein binding of propranolol, glyburide, nicardipine, warfarin, phenytoin, acetylsalicylic acid and tolbutamide in vitro. However, prudent evaluation of individual cases is warranted in the clinical setting.

Certain drugs, including nonsteroidal anti-inflammatory agents (NSAIDs), salicylates, monoamine oxidase inhibitors, and non-selective beta-adrenergic-blocking agents, guanethidine, and CYP2C9 inhibitors (e.g., fluconazole, amiodarone, miconazole, oxandrolone) may potentiate the hypoglycemic action of nateglinide and other oral antidiabetic drugs.

Certain drugs including thiazides, corticosteroids, thyroid products, sympathomimetics, somatropin, rifampin, phenytoin and dietary supplements (St. John’s wort) may reduce the hypoglycemic action of nateglinide and other oral antidiabetic drugs. Somatostatin analogues may potentiate or attenuate the hypoglycemic action of nateglinide.

When these drugs are administered to or withdrawn from patients receiving nateglinide, the patient should be observed closely for changes in glycemic control.

Drug/Food Interactions

The pharmacokinetics of nateglinide were not affected by the composition of a meal (high protein, fat, or carbohydrate). However, peak plasma levels were significantly reduced when nateglinide was administered 10 minutes prior to a liquid meal. Nateglinide did not have any effect on gastric emptying in healthy subjects as assessed by acetaminophen testing.

Carcinogenesis and Mutagenesis and Impairment of Fertility

Carcinogenicity: A two-year carcinogenicity study in Sprague-Dawley rats was performed with oral doses of nateglinide up to 900 mg/kg/day, which produced AUC exposures in male and female rats approximately 30 and 40 times the human therapeutic exposure respectively with a recommended nateglinide dose of 120 mg, three times daily before meals. A two-year carcinogenicity study in B6C3F1 mice was performed with oral doses of nateglinide up to 400 mg/kg/day, which produced AUC exposures in male and female mice approximately 10 and 30 times the human therapeutic exposure with a recommended nateglinide dose of 120 mg, three times daily before meals. No evidence of a tumorigenic response was found in either rats or mice.

Mutagenesis: Nateglinide was not genotoxic in the in vitro Ames test, mouse lymphoma assay, chromosome aberration assay in Chinese hamster lung cells, or in the in vivo mouse micronucleus test.

Impairment of Fertility: Fertility was unaffected by administration of nateglinide to rats at doses up to 600 mg/kg (approximately 16 times the human therapeutic exposure with a recommended nateglinide dose of 120 mg three times daily before meals).

Pregnancy

Pregnancy Category C:

Nateglinide was not teratogenic in rats at doses up to 1000 mg/kg (approximately 60 times the human therapeutic exposure with a recommended nateglinide dose of 120 mg, three times daily before meals). In the rabbit, embryonic development was adversely affected and the incidence of gallbladder agenesis or small gallbladder was increased at a dose of 500 mg/kg (approximately 40 times the human therapeutic exposure with a recommended nateglinide dose of 120 mg, three times daily before meals). There are no adequate and well-controlled studies in pregnant women. Nateglinide should not be used during pregnancy.

Labor and Delivery

The effect of nateglinide on labor and delivery in humans is not known.

Nursing Mothers

Studies in lactating rats showed that nateglinide is excreted in the milk; the AUC 0-48h ratio in milk to plasma was approximately 1:4. During the peri- and postnatal period body weights were lower in offspring of rats administered nateglinide at 1000 mg/kg (approximately 60 times the human therapeutic exposure with a recommended nateglinide dose of 120 mg, three times daily before meals). It is not known whether nateglinide is excreted in human milk. Because many drugs are excreted in human milk, nateglinide should not be administered to a nursing woman.

Pediatric Use

Clinical trials to demonstrate the safety and effectiveness in pediatric patients have not been conducted.

Geriatric Use

No differences were observed in safety or efficacy of nateglinide between patients age 65 and over, and those under age 65. However, greater sensitivity of some older individuals to nateglinide therapy cannot be ruled out.

ADVERSE REACTIONS

In clinical trials, approximately 2,600 patients with Type 2 diabetes were treated with nateglinide. Of these, approximately 1,335 patients were treated for 6 months or longer and approximately 190 patients for one year or longer.

Hypoglycemia was relatively uncommon in all treatment arms of the clinical trials. Only 0.3% of nateglinide patients discontinued due to hypoglycemia. Symptoms suggestive of hypoglycemia have been observed after administration of nateglinide. These symptoms included sweating, trembling, dizziness, increased appetite, palpitations, nausea, fatigue and weakness.

Gastrointestinal symptoms, especially diarrhea and nausea, were no more common in patients using the combination of nateglinide and metformin than in patients receiving metformin alone. Likewise, peripheral edema was no more common in patients using the combination of nateglinide and rosiglitazone than in patients receiving rosiglitazone alone. The following table lists events that occurred more frequently in nateglinide patients than placebo patients in controlled clinical trials.

Common Adverse Events (≥2% in nateglinide patients) in Nateglinide Monotherapy Trials (% of patients)
Preferred Term | Placebo N=458 | Nateglinide N=1441
Upper Respiratory Infection | 8.1 | 10.5
Back Pain | 3.7 | 4.0
Flu Symptoms | 2.6 | 3.6
Dizziness | 2.2 | 3.6
Arthropathy | 2.2 | 3.3
Diarrhea | 3.1 | 3.2
Accidental Trauma | 1.7 | 2.9
Bronchitis | 2.6 | 2.7
Coughing | 2.2 | 2.4
Hypoglycemia | 0.4 | 2.4

During post-marketing experience, rare cases of hypersensitivity reactions such as rash, itching and urticaria have been reported. Similarly, cases of jaundice, cholestatic hepatitis and elevated liver enzymes have been reported.

Laboratory Abnormalities

Uric Acid:There were increases in mean uric acid levels for patients treated with nateglinide alone, nateglinide in combination with metformin, metformin alone, and glyburide alone. The respective differences from placebo were 0.29 mg/dL, 0.45 mg/dL, 0.28 mg/dL, and 0.19 mg/dL. The clinical significance of these findings is unknown.

OVERDOSAGE

In a clinical study in patients with Type 2 diabetes, nateglinide was administered in increasing doses up to 720 mg a day for 7 days and there were no clinically significant adverse events reported. There have been no instances of overdose with nateglinide in clinical trials. However, an overdose may result in an exaggerated glucose-lowering effect with the development of hypoglycemic symptoms. Hypoglycemic symptoms without loss of consciousness or neurological findings should be treated with oral glucose and adjustments in dosage and/or meal patterns. Severe hypoglycemic reactions with coma, seizure, or other neurological symptoms should be treated with intravenous glucose. As nateglinide is highly protein bound, dialysis is not an efficient means of removing it from the blood.

DOSAGE AND ADMINISTRATION

Nateglinide Tablets USP should be taken 1 to 30 minutes prior to meals.

Monotherapy and Combination with Metformin or a Thiazolidinedione

The recommended starting and maintenance dose of nateglinide, alone or in combination with metformin or a thiazolidinedione, is 120 mg three times daily before meals.

The 60 mg dose of nateglinide, either alone or in combination with metformin or a thiazolidinedione, may be used in patients who are near goal HbA1c when treatment is initiated.

Dosage in Geriatric Patients

No special dose adjustments are usually necessary. However, greater sensitivity of some individuals to nateglinide therapy cannot be ruled out.

Dosage in Renal and Hepatic Impairment

No dosage adjustment is necessary in patients with mild-to-severe renal insufficiency or in patients with mild hepatic insufficiency. Dosing of patients with moderate-to-severe hepatic dysfunction has not been studied. Therefore, nateglinide should be used with caution in patients with moderate-to-severe liver disease (see PRECAUTIONS, Hepatic Impairment).

HOW SUPPLIED

Nateglinide Tablets, USP

120 mg

Orange color coated, oval shaped biconvex, tablet debossed with “P 985” on one side and plain on the other side

Bottles of 10……………NDC 54868-6255-0

Bottles of 90……………NDC 54868-6255-1

Storage

Store at 25°C (77°F); excursions permitted to 15°C to 30°C (59°F to 86°F). [See USP Controlled Room Temperature].

Dispense in a tight, light resistant containers.

Manufactured by:

Par Pharmaceutical Companies, Inc.

Spring Valley, NY 10977

R09/2011

Relabeling and Repackaging by:
Physicians Total Care, Inc.
Tulsa, Oklahoma 74146